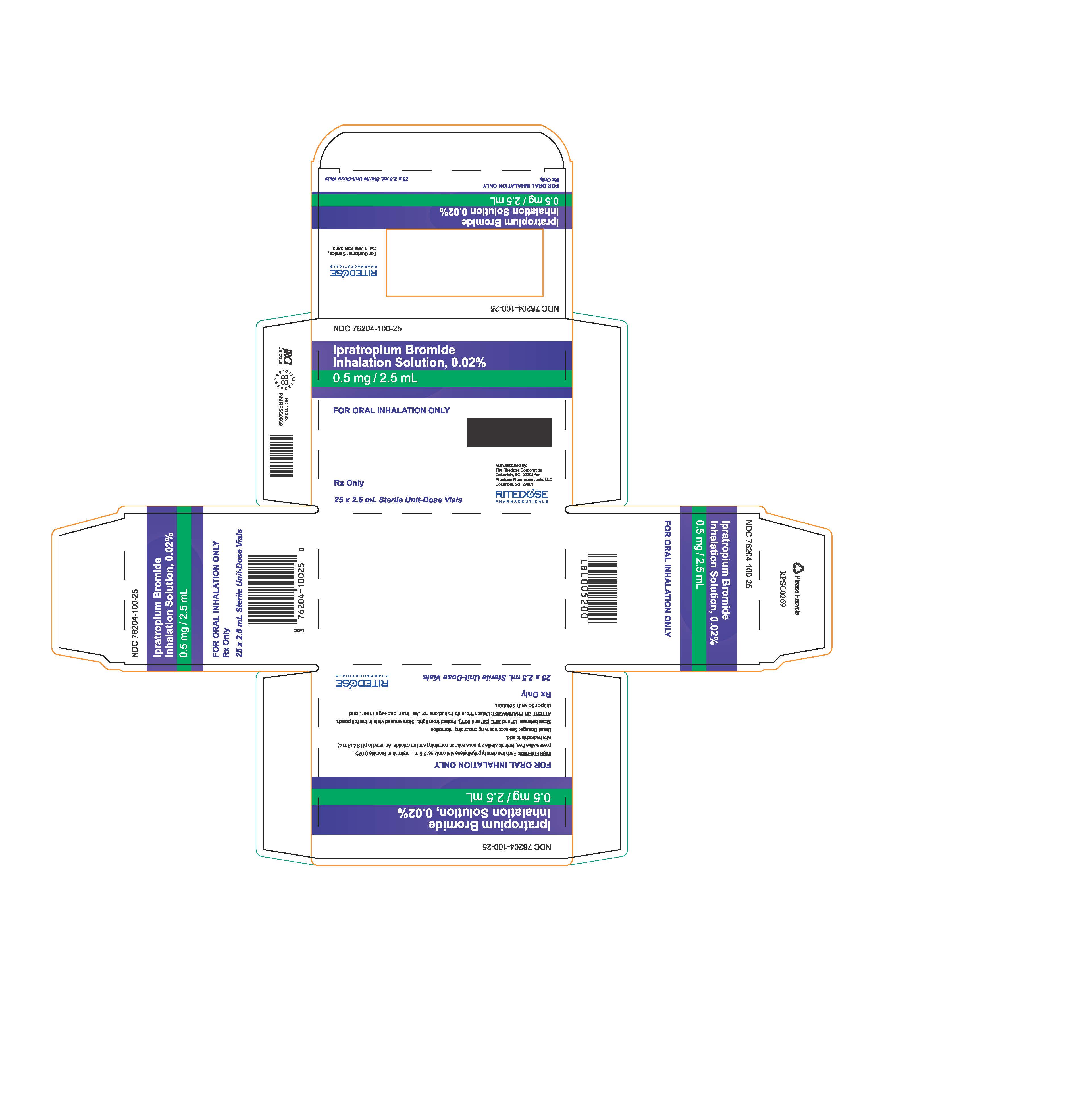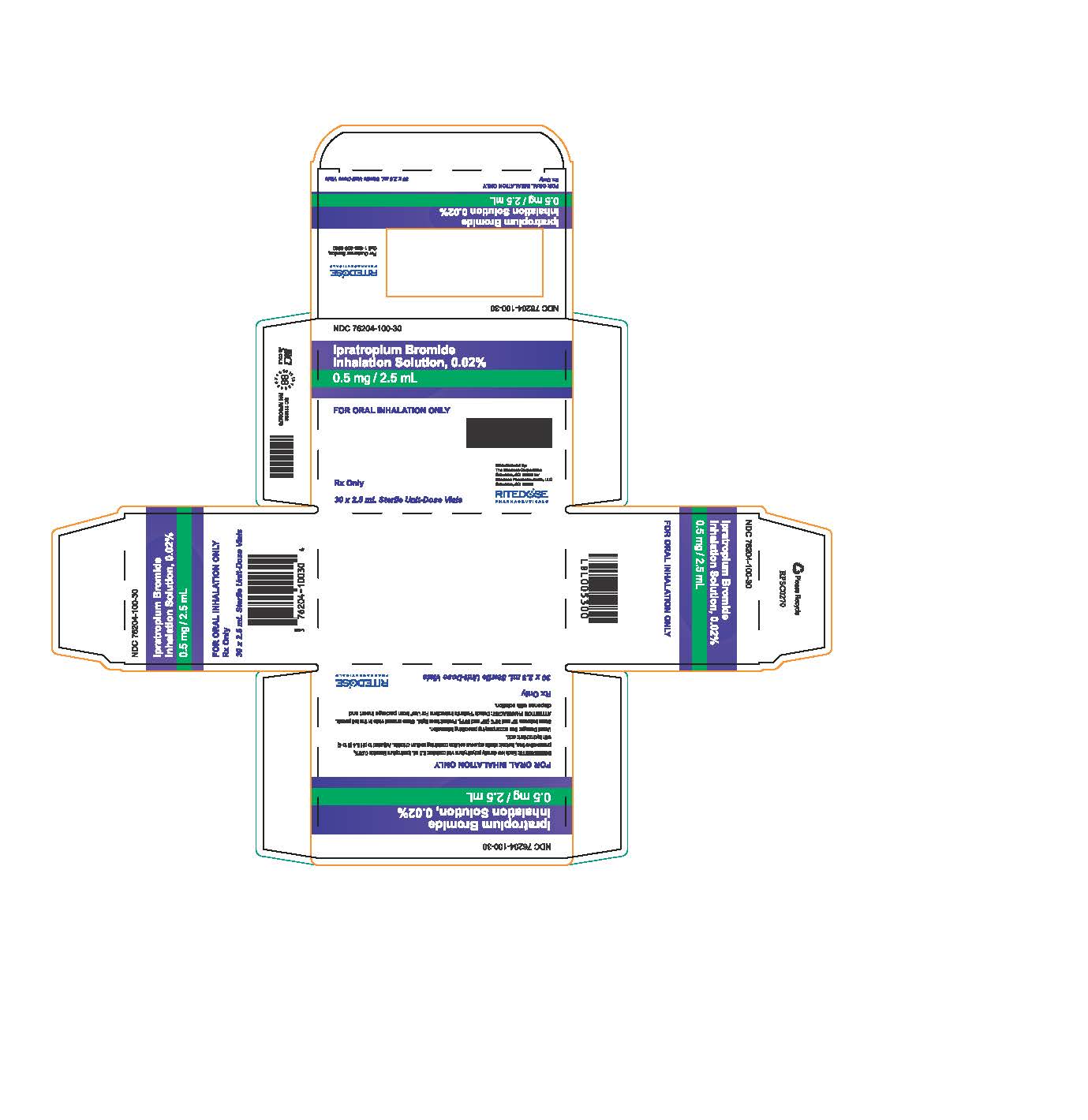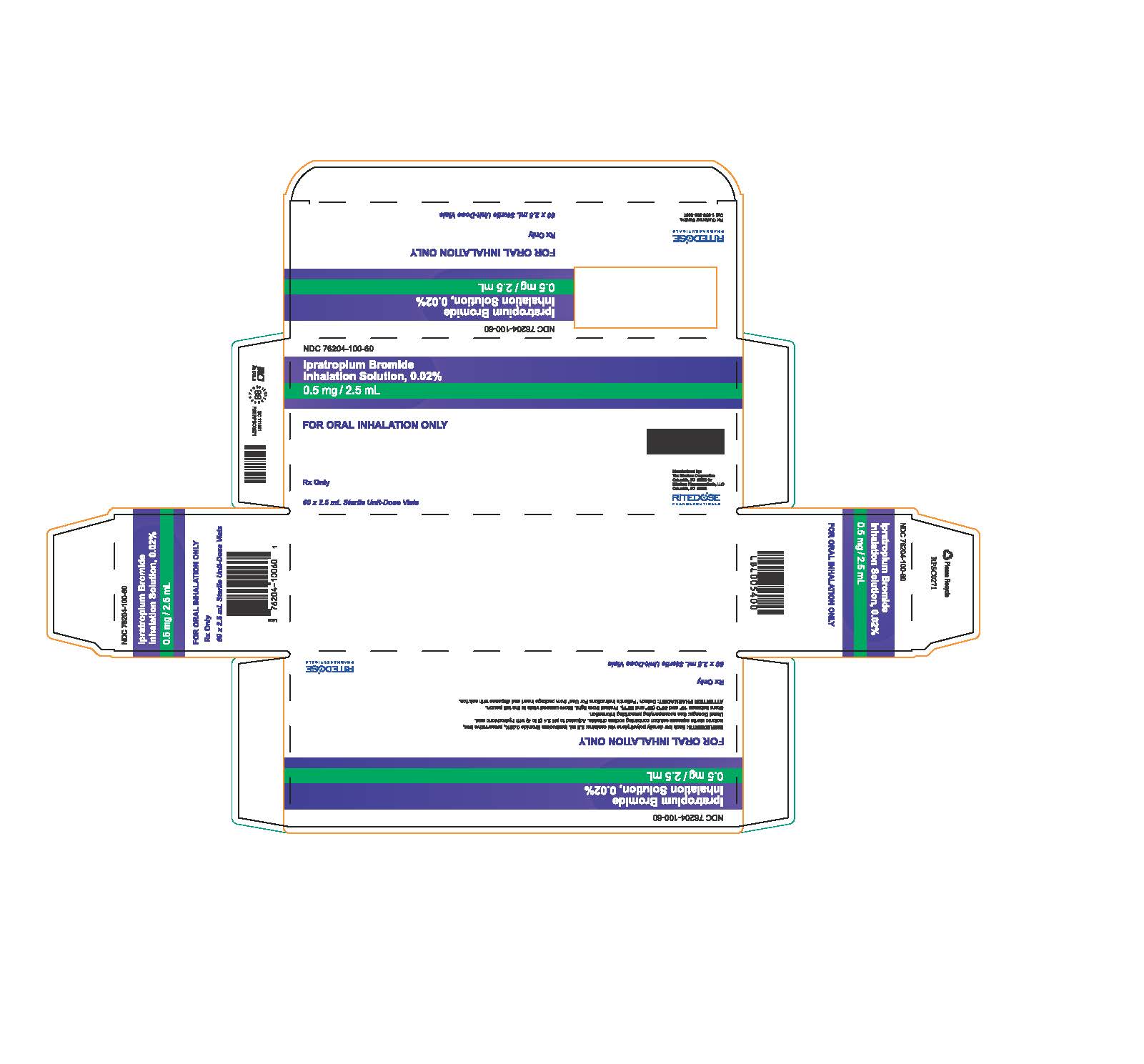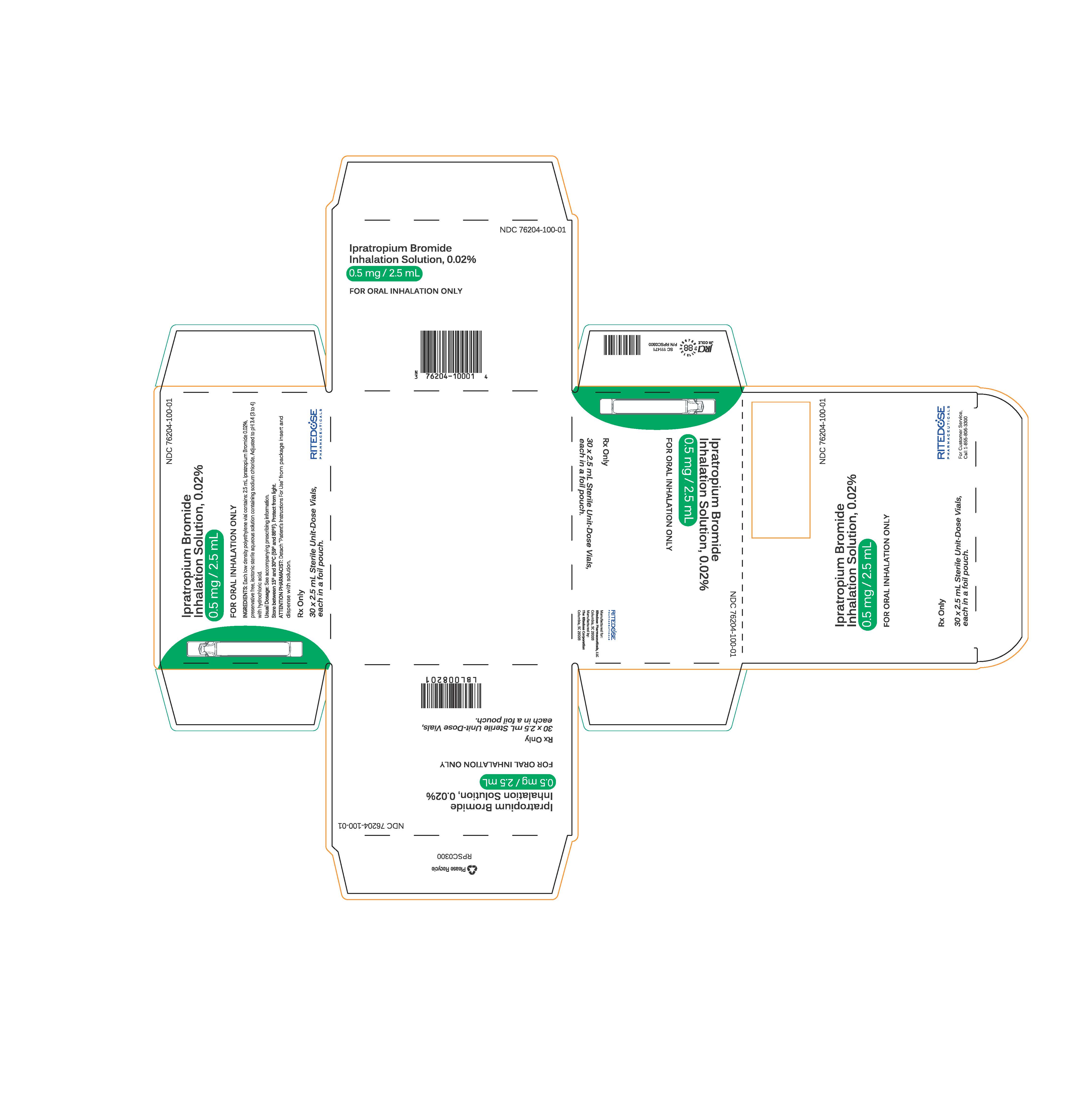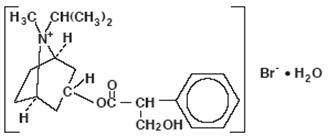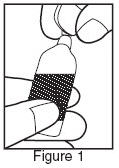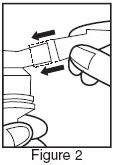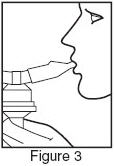 DRUG LABEL: Ipratropium Bromide
NDC: 76204-100 | Form: SOLUTION
Manufacturer: Ritedose Pharmaceuticals, LLC
Category: prescription | Type: HUMAN PRESCRIPTION DRUG LABEL
Date: 20251210

ACTIVE INGREDIENTS: IPRATROPIUM BROMIDE 0.5 mg/2.5 mL
INACTIVE INGREDIENTS: SODIUM CHLORIDE; HYDROCHLORIC ACID; WATER

Ipratropium Bromide Inhalation Solution 0.02% (RDP)

Prescribing Information

Rx Only

DESCRIPTION

The active ingredient, ipratropium bromide monohydrate, USP, is an anticholinergic bronchodilator chemically described as 8-azoniabicyclo [3.2.1]- octane, 3-(3-hydroxy-1-oxo-2-phenylpropoxy)-8-methyl-8-(1-methylethyl)-, bromide, monohydrate (endo, syn)-, (±)-; a synthetic quaternary ammonium compound, chemically related to atropine.

Ipratropium Bromide Monohydrate C20H30BrNO3•H2O Mol.Wt. 430.4

Ipratropium bromide is a white crystalline substance, freely soluble in water and lower alcohols. It is a quaternary ammonium compound and thus exists in an ionized state in aqueous solutions. It is relatively insoluble in non-polar media.

Ipratropium Bromide Inhalation Solution is administered by oral inhalation with the aid of a nebulizer. It contains ipratropium bromide, USP 0.02% (anhydrous basis) in a sterile, preservative-free, isotonic saline solution, pH-adjusted to 3.4 (3 to 4) with hydrochloric acid.

CLINICAL PHARMACOLOGY

Ipratropium bromide is an anticholinergic (parasympatholytic) agent that, based on animal studies, appears to inhibit vagally mediated reflexes by antagonizing the action of acetylcholine, the transmitter agent released from the vagus nerve.

Anticholinergics prevent the increases in intracellular concentration of cyclic guanosine monophosphate (cyclic GMP) that are caused by interaction of acetylcholine with the muscarinic receptor on bronchial smooth muscle.

The bronchodilation following inhalation of ipratropium bromide is primarily a local, site-specific effect, not a systemic one. Much of an administered dose is swallowed but not absorbed, as shown by fecal excretion studies. Following nebulization of a 2 mg dose, a mean 7% of the dose was absorbed into the systemic circulation either from the surface of the lung or from the gastrointestinal tract. The half-life of elimination is about 1.6 hours after intravenous administration. Ipratropium bromide is minimally (0 to 9% in vitro) bound to plasma albumin and a1-acid glycoproteins. It is partially metabolized. Autoradiographic studies in rats have shown that ipratropium bromide does not penetrate the blood-brain barrier. Ipratropium bromide has not been studied in patients with hepatic or renal insufficiency. It should be used with caution in those patient populations.

In controlled 12-week studies in patients with bronchospasm associated with chronic obstructive pulmonary disease (chronic bronchitis and emphysema) significant improvements in pulmonary function (FEV1 increases of 15% or more) occurred within 15 to 30 minutes, reached a peak in 1 to 2 hours, and persisted for periods of 4 to 5 hours in the majority of patients, with about 25% to 38% of the patients demonstrating increases of 15% or more for at least 7 to 8 hours. Continued effectiveness of ipratropium bromide inhalation solution was demonstrated throughout the 12-week period. In addition, significant increases in forced vital capacity (FVC) have been demonstrated. However, ipratropium bromide did not consistently produce significant improvement in subjective symptom scores nor in quality of life scores over the 12-week duration of study.

Additional controlled 12-week studies were conducted to evaluate the safety and effectiveness of ipratropium bromide inhalation solution administered concomitantly with the beta adrenergic bronchodilator solutions metaproterenol and albuterol compared with the administration of each of the beta agonists alone. Combined therapy produced significant additional improvement in FEV1 and FVC. On combined therapy, the median duration of 15% improvement in FEV1 was 5 to 7 hours, compared with 3 to 4 hours in patients receiving a beta agonist alone.

INDICATIONS AND USAGE

Ipratropium Bromide Inhalation Solution administered either alone or with other bronchodilators, especially beta adrenergics, is indicated as a bronchodilator for maintenance treatment of bronchospasm associated with chronic obstructive pulmonary disease, including chronic bronchitis and emphysema.

CONTRAINDICATIONS

Ipratropium bromide is contraindicated in known or suspected cases of hypersensitivity to ipratropium bromide, or to atropine and its derivatives.

WARNINGS

The use of ipratropium bromide inhalation solution as a single agent for the relief of bronchospasm in acute COPD exacerbation has not been adequately studied. Drugs with faster onset of action may be preferable as initial therapy in this situation. Combination of ipratropium bromide and beta agonists has not been shown to be more effective than either drug alone in reversing the bronchospasm associated with acute COPD exacerbation.

Immediate hypersensitivity reactions may occur after administration of ipratropium bromide, as demonstrated by rare cases of urticaria, angioedema, rash, bronchospasm and oropharyngeal edema.

PRECAUTIONS

General

Ipratropium bromide should be used with caution in patients with narrow-angle glaucoma, prostatic hypertrophy or bladder-neck obstruction.

Information for Patients

Patients should be advised that temporary blurring of vision, precipitation or worsening of narrow-angle glaucoma or eye pain may result if the solution comes into direct contact with the eyes. Use of a nebulizer with mouthpiece rather than face mask may be preferable, to reduce the likelihood of the nebulizer solution reaching the eyes. Patients should be advised that ipratropium bromide inhalation solution can be mixed in the nebulizer with albuterol or metaproterenol if used within one hour. Drug stability and safety of Ipratropium Bromide Inhalation Solution when mixed with other drugs in a nebulizer have not been established. Patients should be reminded that ipratropium bromide inhalation solution should be used consistently as prescribed throughout the course of therapy.

Drug Interactions

Ipratropium bromide has been shown to be a safe and effective bronchodilator when used in conjunction with beta adrenergic bronchodilators. Ipratropium bromide has also been used with other pulmonary medications, including methylxanthines and corticosteroids, without adverse drug interactions.

Carcinogenesis, Mutagenesis, Impairment of Fertility

Two-year oral carcinogenicity studies in rats and mice have revealed no carcinogenic potential at dietary doses up to 6 mg/kg/day of ipratropium bromide.

Results of various mutagenicity studies (Ames test, mouse dominant lethal test, mouse micronucleus test and chromosome aberration of bone marrow in Chinese hamsters) were negative.

Fertility of male or female rats at oral doses up to 50 mg/kg/day was unaffected by ipratropium bromide administration. At doses above 90 mg/kg increased resorption and decreased conception rates were observed.

Pregnancy

TERATOGENIC EFFECTS

Pregnancy Category B

Oral reproduction studies performed in mice, rats and rabbits at doses of 10, 100, and 125 mg/kg respectively, and inhalation reproduction studies in rats and rabbits at doses of 1.5 and 1.8 mg/kg (or approximately 38 and 45 times the recommended human daily dose) respectively, have demonstrated no evidence of teratogenic effects as a result of ipratropium bromide. However, no adequate or well-controlled studies have been conducted in pregnant women. Because animal reproduction studies are not always predictive of human response, ipratropium bromide should be used during pregnancy only if clearly needed.

Nursing Mothers

It is not known whether ipratropium bromide is excreted in human milk. Although lipid-insoluble quaternary bases pass into breast milk, it is unlikely that ipratropium bromide would reach the infant to a significant extent, especially when taken by inhalation since ipratropium bromide is not well absorbed systemically after inhalation or oral administration. However, because many drugs are excreted in human milk, caution should be exercised when ipratropium bromide is administered to a nursing woman.

Pediatric Use

Safety and effectiveness in the pediatric population below the age of 12 have not been established.

ADVERSE REACTIONS

Adverse reaction information concerning ipratropium bromide inhalation solution is derived from 12-week active-controlled clinical trials. Additional information is derived from foreign post-marketing experience and the published literature.

All adverse events, regardless of drug relationship, reported by three percent or more patients in the 12-week controlled clinical trials appear in the table below.

Additional adverse reactions reported in less than three percent of the patients treated with ipratropium bromide include tachycardia, palpitations, eye pain, urinary retention, urinary tract infection and urticaria. Cases of precipitation or worsening of narrow-angle glaucoma, mydriasis, and acute eye pain have been reported.

Lower respiratory adverse reactions (bronchitis, dyspnea and bronchospasm) were the most common events leading to discontinuation of ipratropium bromide therapy in the 12-week trials. Headache, mouth dryness and aggravation of COPD symptoms are more common when the total daily dose of ipratropium bromide equals or exceeds 2,000 mcg.

Allergic-type reactions such as skin-rash, angioedema of tongue, lips and face, urticaria, laryngospasm and anaphylactic reaction have been reported. Many of the patients had a history of allergies to other drugs and/or foods.

All Adverse Events, from a Double-blind, Parallel, 12-week Study of patients with COPD [All adverse events, regardless of drug relationship, reported by three percent or more patients in the 12-week controlled clinical trials.]
 | PERCENT OF PATIENTS
 | Ipratropium | Metaproterenol | Ipratropium/ Metaproterenol | Albuterol | Ipratropium/ Albuterol
 | (500 mcg t.i.d.) | (15 mg t.i.d.) | (500 mcg t.i.d./ 15 mg t.i.d.) | (2.5 mg t.i.d.) | (500 mcg t.i.d./ 2.5 mg t.i.d.)
 | n = 219 | n = 212 | n = 108 | n = 205 | n = 100
Body as a Whole-General Disorders
Headache | 6.4 | 5.2 | 6.5 | 6.3 | 9.0
Pain | 4.1 | 3.3 | 0.9 | 2.9 | 5.0
Influenza-like symptoms | 3.7 | 4.7 | 6.5 | 0.5 | 1.0
Back Pain | 3.2 | 1.9 | 1.9 | 2.4 | 0.0
Chest Pain | 3.2 | 4.2 | 5.6 | 2.0 | 1.0
Cardiovascular Disorders
Hypertension/Hypertension Aggravated | 0.9 | 1.9 | 0.9 | 1.5 | 4.0
Central & Peripheral Nervous System
Dizziness | 2.3 | 3.3 | 1.9 | 3.9 | 4.0
Insomnia | 0.9 | 0.5 | 4.6 | 1.0 | 1.0
Tremor | 0.9 | 7.1 | 8.3 | 1.0 | 0.0
Nervousness | 0.5 | 4.7 | 6.5 | 1.0 | 1.0
Gastrointestinal System Disorders
Mouth Dryness | 3.2 | 0.0 | 1.9 | 2.0 | 3.0
Nausea | 4.1 | 3.8 | 1.9 | 2.9 | 2.0
Constipation | 0.9 | 0.0 | 3.7 | 1.0 | 1.0
Musculo-skeletal System Disorders
Arthritis | 0.9 | 1.4 | 0.9 | 0.5 | 3.0
Respiratory System Disorders (Lower)
Coughing | 4.6 | 8.0 | 6.5 | 5.4 | 6.0
Dyspnea | 9.6 | 13.2 | 16.7 | 12.7 | 9.0
Bronchitis | 14.6 | 24.5 | 15.7 | 16.6 | 20.0
Bronchospasm | 2.3 | 2.8 | 4.6 | 5.4 | 5.0
Sputum Increased | 1.4 | 1.4 | 4.6 | 3.4 | 0.0
Respiratory Disorder | 0.0 | 6.1 | 6.5 | 2.0 | 4.0
Respiratory System Disorders (Upper)
Upper Respiratory Tract Infection | 13.2 | 11.3 | 9.3 | 12.2 | 16.0
Pharyngitis | 3.7 | 4.2 | 5.6 | 2.9 | 4.0
Rhinitis | 2.3 | 4.2 | 1.9 | 2.4 | 0.0
Sinusitus | 2.3 | 2.8 | 0.9 | 5.4 | 4.0

OVERDOSAGE

Acute systemic overdosage by inhalation solution is unlikely since ipratropium bromide is not well absorbed after inhalation at up to four-fold the recommended dose, or after oral administration at up to forty-fold the recommended dose. The oral LD50 of ipratropium bromide ranged between 1001 and 2010 mg/kg in mice; between 1667 and 4000 mg/kg in rats; and between 400 and 1300 mg/kg in dogs.

DOSAGE AND ADMINISTRATION

The usual dosage of ipratropium bromide inhalation solution is 500 mcg (1 Unit-Dose Vial) administered three to four times a day by oral nebulization, with doses 6 to 8 hours apart. Ipratropium bromide inhalation solution unit-dose vials contain 500 mcg ipratropium bromide, USP anhydrous in 2.5 mL normal saline. Ipratropium bromide inhalation solution can be mixed in the nebulizer with albuterol or metaproterenol if used within one hour. Drug stability and safety of Ipratropium Bromide Inhalation Solution when mixed with other drugs in a nebulizer have not been established.

HOW SUPPLIED

Ipratropium Bromide Inhalation Solution Unit Dose Vial is supplied as a 0.02% clear, colorless solution containing 2.5 mL.

NDC 76204-100-25, 25 vials per carton / 25 vials per foil pouch

NDC 76204-100-30, 30 vials per carton / 30 vials per foil pouch

NDC 76204-100-01, 30 vials per carton / 1 vial per foil pouch

NDC 76204-100-60, 60 vials per carton / 30 vials per foil pouch

Each vial is made from a low density polyethylene (LDPE) resin.

Vials are supplied in a foil pouch.

STORAGE AND HANDLING

Store between 59°F (15°C) and 86°F (30°C).

Protect from light.

Store unused vials in the foil pouch.

ATTENTION PHARMACIST: Detach "Patient's Instructions for Use" from Package Insert and dispense with solution.

Rx Only

Manufactured by:
The Ritedose Corporation
Columbia, SC 29203 for
Ritedose Pharmaceuticals, LLC
Columbia, SC 29203

To report SUSPECTED ADVERSE
REACTIONS, contact Ritedose
Pharmaceuticals, LLC
at 1-855-806-3300 or FDA
at 1-800-FDA-1088 or www.fda.gov/medwatch

RPIN0044
JAN 2013

Patient's Instructions for Use

Ipratropium Bromide

Inhalation Solution 0.02%

Read complete instructions carefully before using.

1. Twist open the top of one unit dose vial and squeeze the contents into the nebulizer reservoir. (Figure 1).
2. Connect the nebulizer reservoir to the mouthpiece or face mask (Figure 2).
3. Connect the nebulizer to the compressor.
4. Sit in a comfortable, upright position; place the mouthpiece in your mouth (Figure 3) or put on the face mask and turn on the compressor. If a face mask is used, care should be taken to avoid leakage around the mask as temporary blurring of vision, pupil enlargement, precipitation or worsening of narrow angle glaucoma, or eye pain may occur if the solution comes into direct contact with the eyes.
5. Breathe as calmly, deeply, and evenly as possible until no more mist is formed in the nebulizer chamber (about 5 to 15 minutes). At this point, the treatment is finished.
6. Clean the nebulizer (see manufacturer's instructions).

Note: Use only as directed by your physician. More frequent administration or higher doses are not recommended. Ipratropium Bromide Inhalation Solution can be mixed in the nebulizer with albuterol or metaproterenol if used within one hour but not with other drugs. Drug stability and safety of Ipratropium Bromide Inhalation Solution when mixed with other drugs in the nebulizer have not been established.

Store between 59°F (15°C) and 86°F (30°). Protect from light. Store unused vials in the foil pouch.

ADDITIONAL INSTRUCTIONS:
____________________________________
____________________________________
____________________________________
____________________________________
____________________________________
____________________________________
____________________________________

Manufactured by:
The Ritedose Corporation
Columbia, SC 29203 for
Ritedose Pharmaceuticals, LLC
Columbia, SC 29203

To report SUSPECTED ADVERSE
REACTIONS, contact Ritedose
Pharmaceuticals, LLC
at 1-855-806-3300 or FDA
at 1-800-FDA-1088 or www.fda.gov/medwatch

JAN 2013

PRINCIPAL DISPLAY PANEL - RDP 25 ct Brick Carton

NDC 76204-100-25

Ipratropium Bromide Inhalation Solution, 0.02%
0.5 mg / 2.5 mL

FOR ORAL INHALATION ONLY

INGREDIENTS: Each low density polyethylene vial contains: 2.5 mL Ipratropium Bromide 0.02%, preservative free, isotonic sterile aqueous solution containing sodium chloride. Adjusted to pH 3.4 (3 to 4) with hydrochloric acid.
Usual Dosage: See accompanying prescribing information.
Store between 15° and 30°C (59° and 86°F). Protect from light. Store unused vials in the foil pouch.
ATTENTION PHARMACIST: Detach "Patient's Instructions For Use" from package insert and dispense with solution.

Rx Only

25 x 2.5 mL Sterile Unit-Dose Vials

PRINCIPAL DISPLAY PANEL - RDP 30 ct Brick Carton

NDC 76204-100-30

Ipratropium Bromide Inhalation Solution, 0.02%
0.5 mg / 2.5 mL

FOR ORAL INHALATION ONLY

INGREDIENTS: Each low density polyethylene vial contains: 2.5 mL Ipratropium Bromide 0.02%, preservative free, isotonic sterile aqueous solution containing sodium chloride. Adjusted to pH 3.4 (3 to 4) with hydrochloric acid.
Usual Dosage: See accompanying prescribing information.
Store between 15° and 30°C (59° and 86°F). Protect from light. Store unused vials in the foil pouch.
ATTENTION PHARMACIST: Detach "Patient's Instructions For Use" from package insert and dispense with solution.

Rx Only

30 x 2.5 mL Sterile Unit-Dose Vials

PRINCIPAL DISPLAY PANEL - RDP 60 ct Brick Carton

NDC 76204-100-60

Ipratropium Bromide Inhalation Solution, 0.02%
0.5 mg / 2.5 mL

FOR ORAL INHALATION ONLY

INGREDIENTS: Each low density polyethylene vial contains: 2.5 mL Ipratropium Bromide 0.02%, preservative free, isotonic sterile aqueous solution containing sodium chloride. Adjusted to pH 3.4 (3 to 4) with hydrochloric acid.
Usual Dosage: See accompanying prescribing information.
Store between 15° and 30°C (59° and 86°F). Protect from light. Store unused vials in the foil pouch.
ATTENTION PHARMACIST: Detach "Patient's Instructions For Use" from package insert and dispense with solution.

Rx Only

60 x 2.5 mL Sterile Unit-Dose Vials

PRINCIPAL DISPLAY PANEL - RDP 30 ct Singles Carton

NDC 76204-100-01

Ipratropium Bromide Inhalation Solution, 0.02%
0.5 mg / 2.5 mL

FOR ORAL INHALATION ONLY

INGREDIENTS: Each low density polyethylene vial contains: 2.5 mL Ipratropium Bromide 0.02%, preservative free, isotonic sterile aqueous solution containing sodium chloride. Adjusted to pH 3.4 (3 to 4) with hydrochloric acid.
Usual Dosage: See accompanying prescribing information.
Store between 15° and 30°C (59° and 86°F). Protect from light.
ATTENTION PHARMACIST: Detach "Patient's Instructions For Use" from package insert and dispense with solution.

Rx Only

30 x 2.5 mL Sterile Unit-Dose Vials, each in a foil pouch